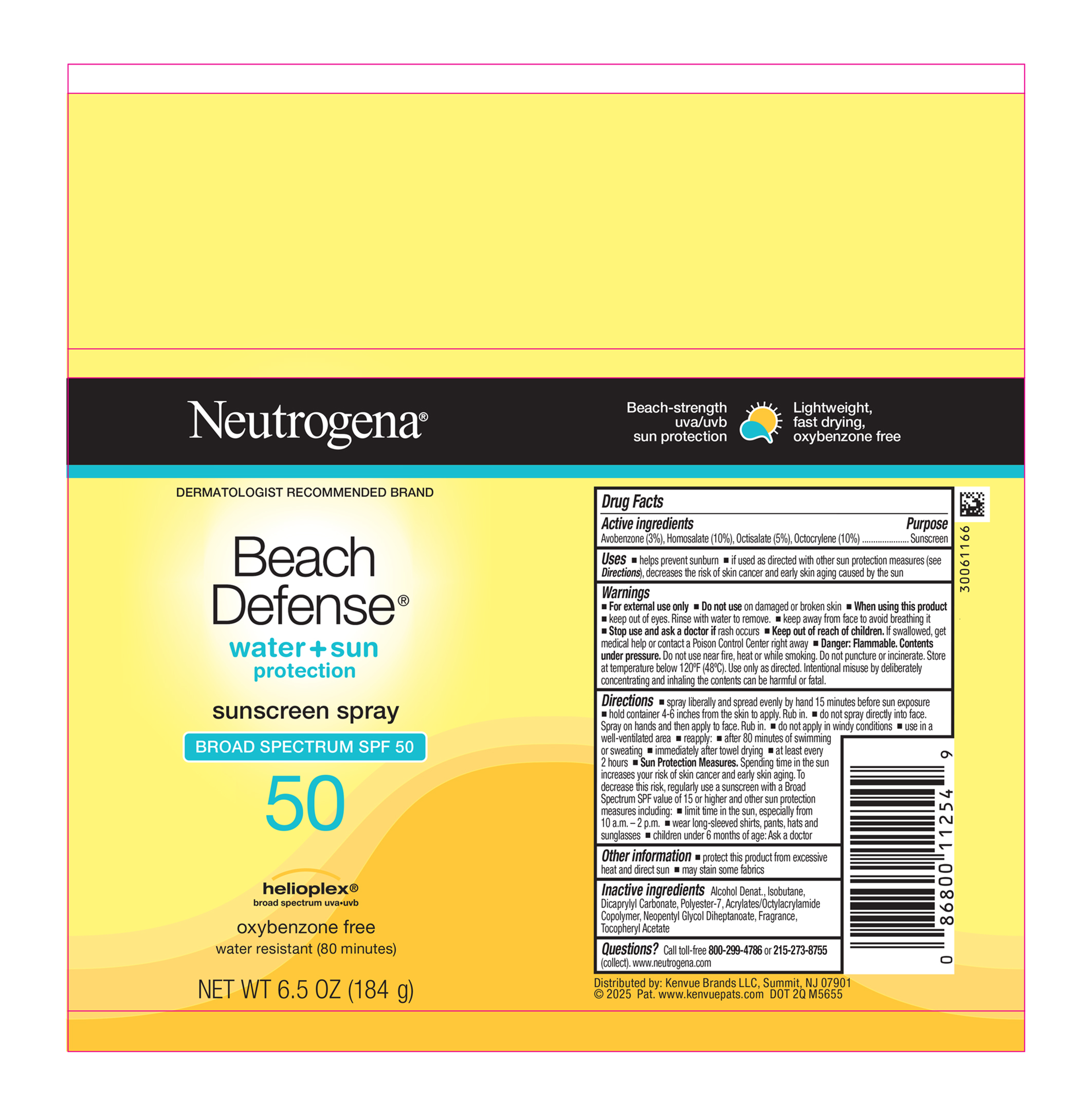 DRUG LABEL: Neutrogena Beach Defense Water Plus Sun Protection Sunscreen Broad Spectrum SPF 50
NDC: 69968-0600 | Form: SPRAY
Manufacturer: Kenvue Brands LLC
Category: otc | Type: HUMAN OTC DRUG LABEL
Date: 20251106

ACTIVE INGREDIENTS: AVOBENZONE 30 mg/1 g; HOMOSALATE 100 mg/1 g; OCTISALATE 50 mg/1 g; OCTOCRYLENE 100 mg/1 g
INACTIVE INGREDIENTS: ALCOHOL; ISOBUTANE; DICAPRYLYL CARBONATE; POLYESTER-7; NEOPENTYL GLYCOL DIHEPTANOATE; .ALPHA.-TOCOPHEROL ACETATE; ACRYLATE/ISOBUTYL METHACRYLATE/N-TERT-OCTYLACRYLAMIDE COPOLYMER (75000 MW)

Neutrogena® Beach Defense® water + sun protection sunscreen spray BROAD SPECTRUM SPF50

Drug Facts

ACTIVE INGREDIENT

Active ingredients | Purpose
Avobenzone 3% | Sunscreen
Homosalate 10% | Sunscreen
Octisalate 5% | Sunscreen
Octocrylene 10% | Sunscreen

Uses

- helps prevent sunburn
- if used as directed with other sun protection measures (see Directions), decreases the risk of skin cancer and early skin aging caused by the sun

Warnings

- For external use only
- Do not use on damaged or broken skin
- When using this product
- keep out of eyes. Rinse with water to remove.
- keep away from face to avoid breathing it
- Stop use and ask a doctor if rash occurs

- Keep out of reach of children. If swallowed, get medical help or contact a Poison Control Center right away
- Danger: Flammable. Contents under pressure. Do not use near fire, heat or while smoking. Do not puncture or incinerate. Store at temperature below 120°F (48°C). Use only as directed. Intentional misuse by deliberately concentrating and inhaling the contents can be harmful or fatal.

Directions

- spray liberally and spread evenly by hand 15 minutes before sun exposure
- hold container 4-6 inches from the skin to apply. Rub in.
- do not spray directly into face. Spray on hands and then apply to face. Rub in.
- do not apply in windy conditions
- use in a well-ventilated area
- reapply:
- after 80 minutes of swimming or sweating
- immediately after towel drying
- at least every 2 hours
- Sun Protection Measures. Spending time in the sun increases your risk of skin cancer and early skin aging. To decrease this risk, regularly use a sunscreen with a Broad Spectrum SPF value of 15 or higher and other sun protection measures including:
- limit time in the sun, especially from 10 a.m. – 2 p.m.
- wear long-sleeved shirts, pants, hats, and sunglasses
- children under 6 months of age: Ask a doctor

Other information

- protect this product from excessive heat and direct sun
- may stain some fabrics

Inactive ingredients

Alcohol Denat., Isobutane, Dicaprylyl Carbonate, Polyester-7, Acrylates/Octylacrylamide Copolymer, Neopentyl Glycol Diheptanoate, Fragrance, Tocopheryl Acetate

Questions or Comments?

Call toll-free 800-299-4786 or 215-273-8755 (collect). www.neutrogena.com

Distributed by:

Kenvue Brands LLC
Summit, NJ 07901

PRINCIPAL DISPLAY PANEL - 184 g Can Label

Neutrogena®
DERMATOLOGIST RECOMMENDED BRAND

Beach
Defense®
water + sun
protection

sunscreen spray
BROAD SPECTRUM SPF 50

50

helioplex®
broad spectrum uva•uvb

oxybenzone free
water resistant (80 minutes)

NET WT 6.5 OZ (184 g)